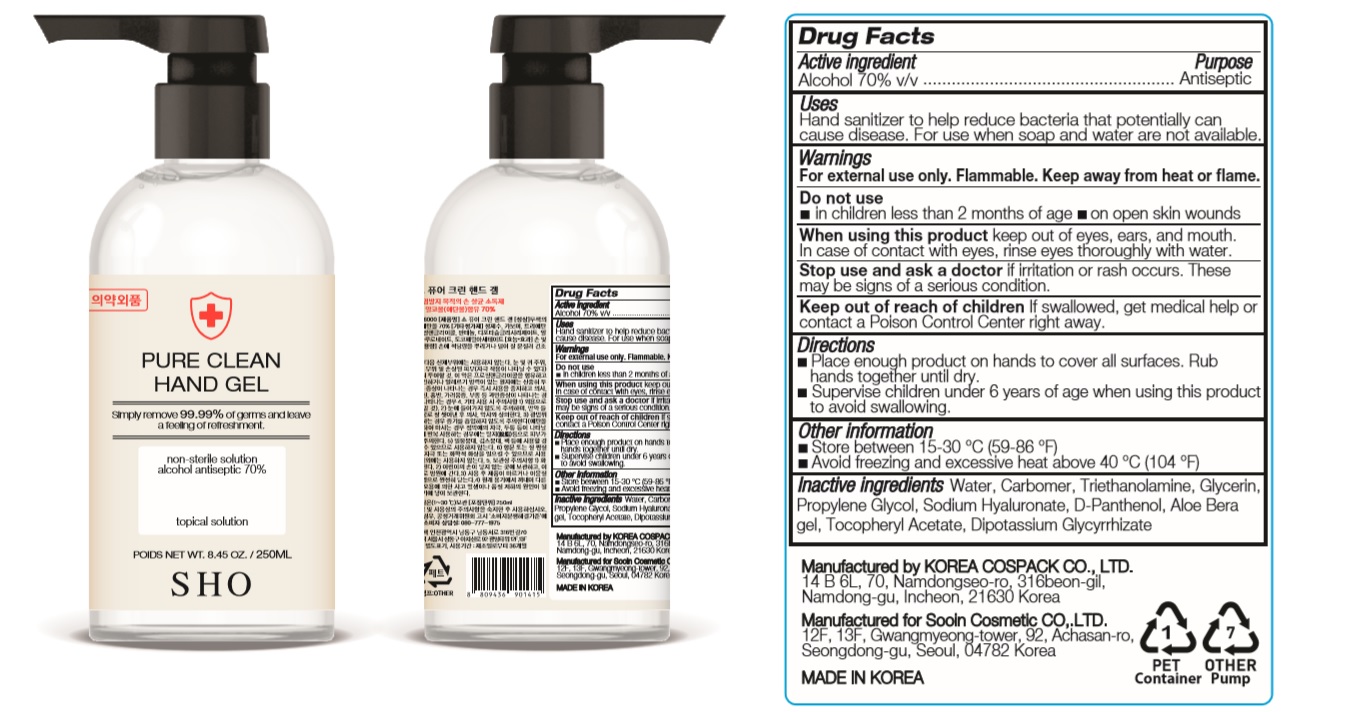 DRUG LABEL: SHO PURE CLEAN HAND Gel
NDC: 74064-2525 | Form: GEL
Manufacturer: KOREA COSPACK CO.,LTD.
Category: otc | Type: HUMAN OTC DRUG LABEL
Date: 20200427

ACTIVE INGREDIENTS: ALCOHOL 175 mL/250 mL
INACTIVE INGREDIENTS: TROLAMINE; PROPYLENE GLYCOL; GLYCERIN; GLYCYRRHIZINATE DIPOTASSIUM; WATER; DEXPANTHENOL; HYALURONATE SODIUM; ALOE VERA LEAF; CARBOMER HOMOPOLYMER, UNSPECIFIED TYPE; .ALPHA.-TOCOPHEROL ACETATE

SHO PURE CLEAN HAND Gel 250 ml : 74064-2525